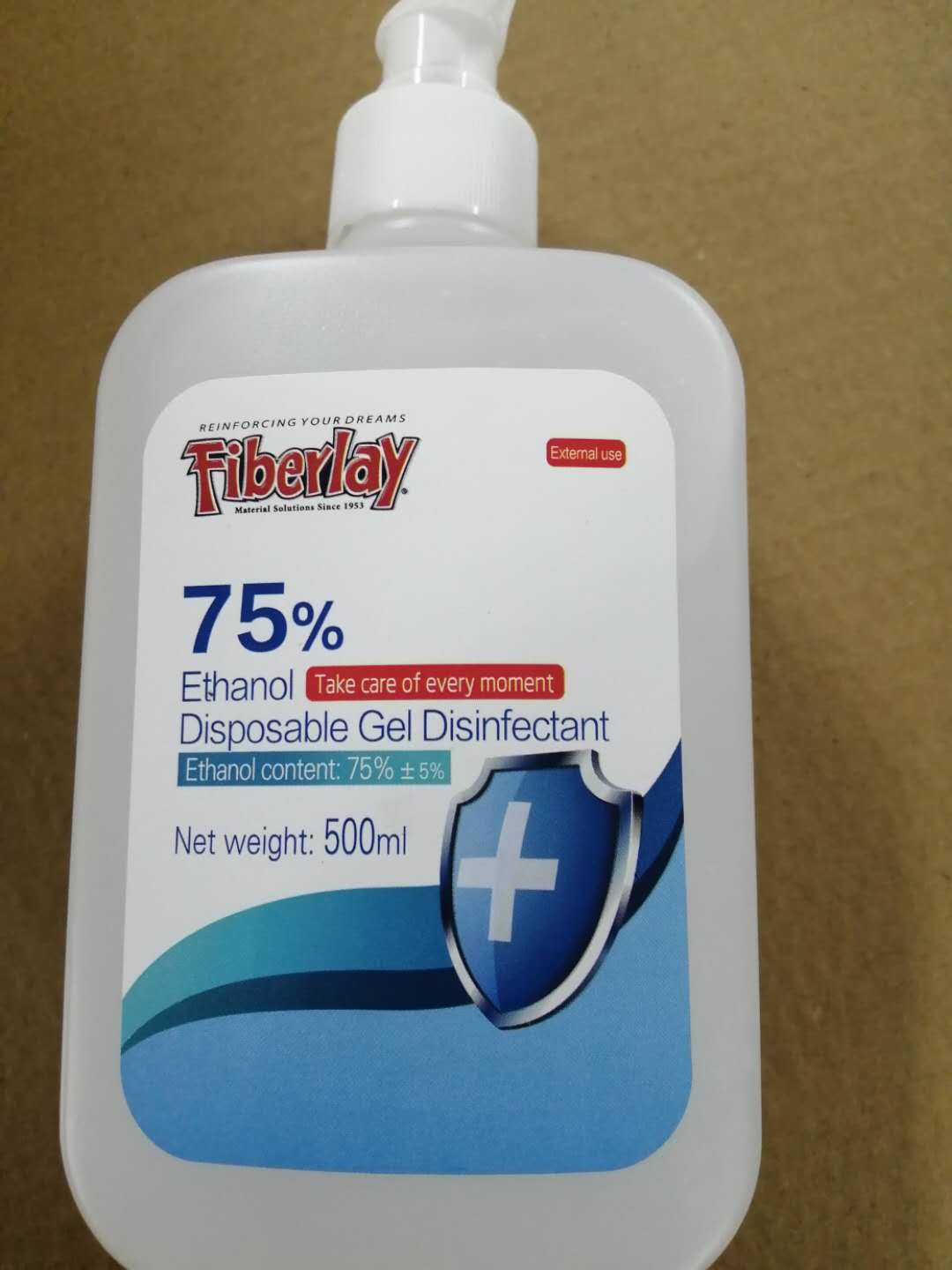 DRUG LABEL: Fiberlay Ethanol Disposable Gel Disinfectant
NDC: 53048-001 | Form: GEL
Manufacturer: SHANDONG LUGANGFUYOU MEDICAL CO., LTD
Category: otc | Type: HUMAN OTC DRUG LABEL
Date: 20200522

ACTIVE INGREDIENTS: ALCOHOL 375 mL/500 mL
INACTIVE INGREDIENTS: CARBOMER HOMOPOLYMER, UNSPECIFIED TYPE; GLYCERIN; WATER

DOSAGE AND ADMINISTRATION

Protect from light and store ina cool, dry, venilatdplace.

INACTIVE INGREDIENT

Deionized water

Glycerine

Carbomer

INDICATIONS AND USAGE

1.Hygiene hands: Take an aprpiate amount of hand dsinfectant on the palm of your hands, rub your hands together for 1 minute to dsinfect.
2. Surgical hands: After surgical hand washing take an apropiate amount of hand dsinfecant and evenly apply it to the skin of the hands, forearm and lower third of the upper arm for 3min.
3. Skin: Apply the skin surface evenly for 3min.

ACTIVE INGREDIENT

Ethanol

keep out of reach of children

PURPOSE

Disinfection
Sterilization
No Rinseing

WARNINGS

1.This is an extemal use dinfectant, please do not take titemallKeep itout of reach of children.

2. This product is fanmmable and away from fre sources.

3. Use with caution to those who are alergic to alcohol.

4. Protect from light and store ina cool, dry, venilatdplace.

5. Avoid couse withantagonist dugs.